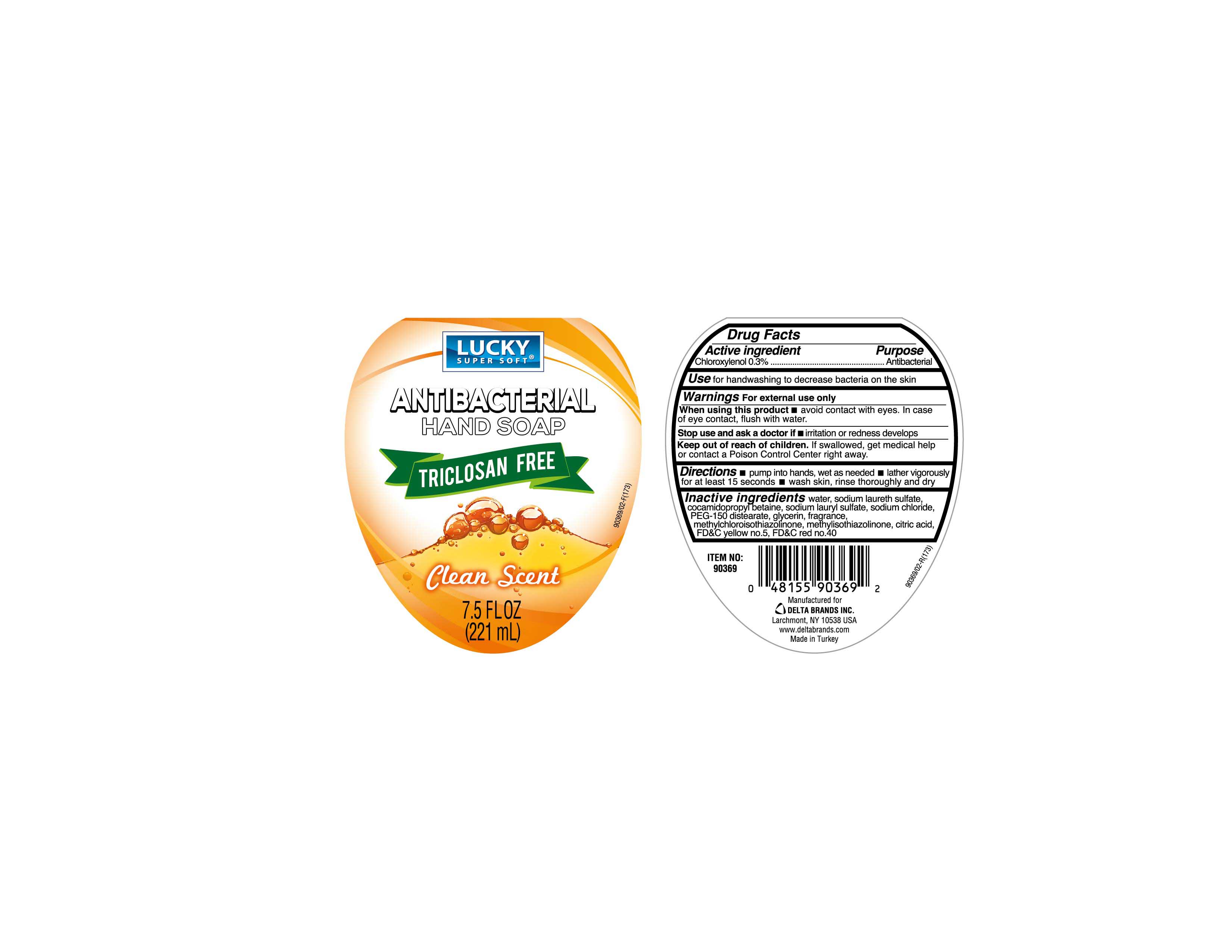 DRUG LABEL: LUCKY
NDC: 20276-151 | Form: LIQUID
Manufacturer: Delta Brands Inc
Category: otc | Type: HUMAN OTC DRUG LABEL
Date: 20230622

ACTIVE INGREDIENTS: CHLOROXYLENOL 0.3 g/100 mL
INACTIVE INGREDIENTS: CITRIC ACID MONOHYDRATE; AMMONIUM LAURYL SULFATE; EDETATE SODIUM TETRAHYDRATE; WATER; FD&C RED NO. 40; COCAMIDOPROPYL BETAINE; AMMONIUM CHLORIDE; DMDM HYDANTOIN; FD&C YELLOW NO. 5

LuckyHndSoapChlrxynl

Active ingredient

Chloroxylenol 0.3%

Purpose

Antibacterial

Use

for handwashing to decrease bacteria on the skin

Warnings

For external use only

When using this product

■ avoid contact with the eyes. In case of eye contact, flush with water.

Stop use and ask a doctor if

■ irritation and redness develops

Keep out of reach of children

If swallowed, get medical help or contact a Poison Control Center right away.

Directions

■ pump into hands, wet as needed ■ lather vigorously for at least 15 seconds ■ wash skin, rinse thoroughly and dry

Inactive ingredients

water (aqua), ammonium lauryl sulfate, cocamidopropyl betaine, ammonium chloride, DMDM hydantoin, fragrance, citric acid, tetrasodium EDTA, FD&C yellow no. 5, FD&C red no. 40